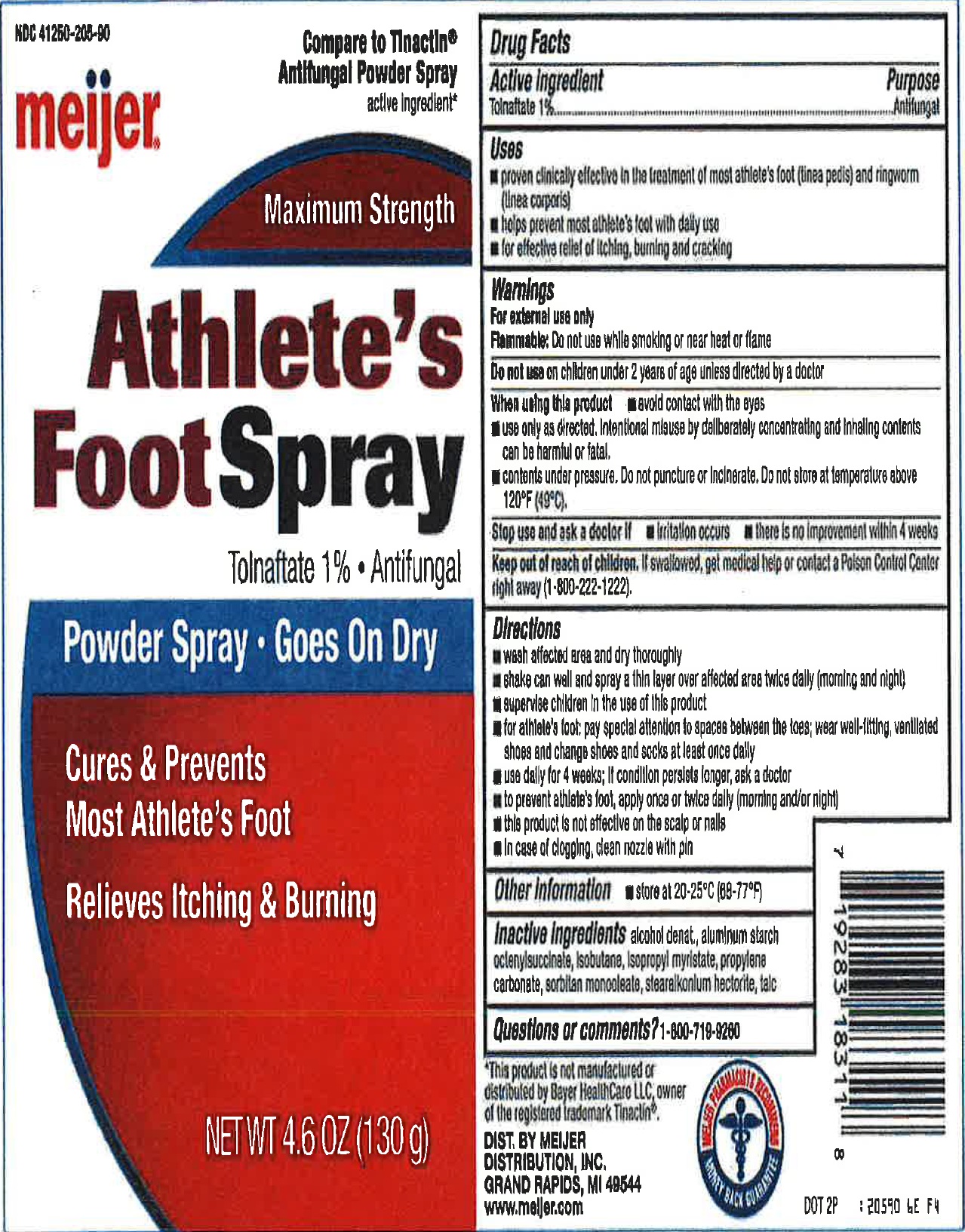 DRUG LABEL: Meijer Maximum Strength Anthletes foot Antifungal
NDC: 23667-810 | Form: SPRAY
Manufacturer: Formulated Solutions, LLC
Category: otc | Type: HUMAN OTC DRUG LABEL
Date: 20231202

ACTIVE INGREDIENTS: TOLNAFTATE 10 mg/1 g
INACTIVE INGREDIENTS: ALCOHOL; ALUMINUM STARCH OCTENYLSUCCINATE; ISOBUTANE; ISOPROPYL MYRISTATE; PROPYLENE CARBONATE; SORBITAN MONOOLEATE; STEARALKONIUM HECTORITE; TALC

Meijer Maximum Strength Anthlete's foot Tolnaftate Antifungal

Active ingredient

Tolnaftate 1%

Purpose

Antifungal

Uses

- proven clinically effective in the treatment of most athlet's foot (tinea pedis) and ringworm (tinea corporis)
- helps prevent most athlete's foot with daily use
- for effective relief if itching, burning, cracking

Warnings

For external use only

Flammable: Do not use while smoking or near heat or flame

Do not use

on children under 2 years of age unless directed by a doctor

When using this product

- avoid contact with the eyes
- use only as directed intentional misuse by deliberately concentrating and inhaling contents can be harmful or fatal
- contents under pressure. Do not punture or incinerate. Do not store at temperature above 120°F (49°C).

Stop use and ask a doctor if

- irritation occurs
- there is no improvement within 4 weeks

Keep out of reach of children.

If swallowed, get medical help or contact a Poison Control Center right away (1-800-222-1222).

Directions

- wash affected area and dry thoroughly
- shake can well and spray a thin layer over affected area twice daily (morning and night)
- supervise children in the use of this product
- for athlete's foot: pay special attention to spaces between the toas, wear well-fitting, ventilated shoes and change shoes and sucks at least once daily
- use daily for 4 weeks; if condition persist longer, ask a doctor
- to prevent athlete's foot, apply once or twice daily (morning and/or night)
- this product is not effective on the scalp or nails
- In case of clogging, clean nozzle with pin

Other information

store at 20-25°C (68-77°F)

Inactive Ingredients

alcohol denat, aluminum starch octenylsuccinate, isobutane, isopropyl myristate, propylene carbonate, sorbitan monooleate, stearalkonium hectorite, talc

Questions or comments?

1-800-719-9260